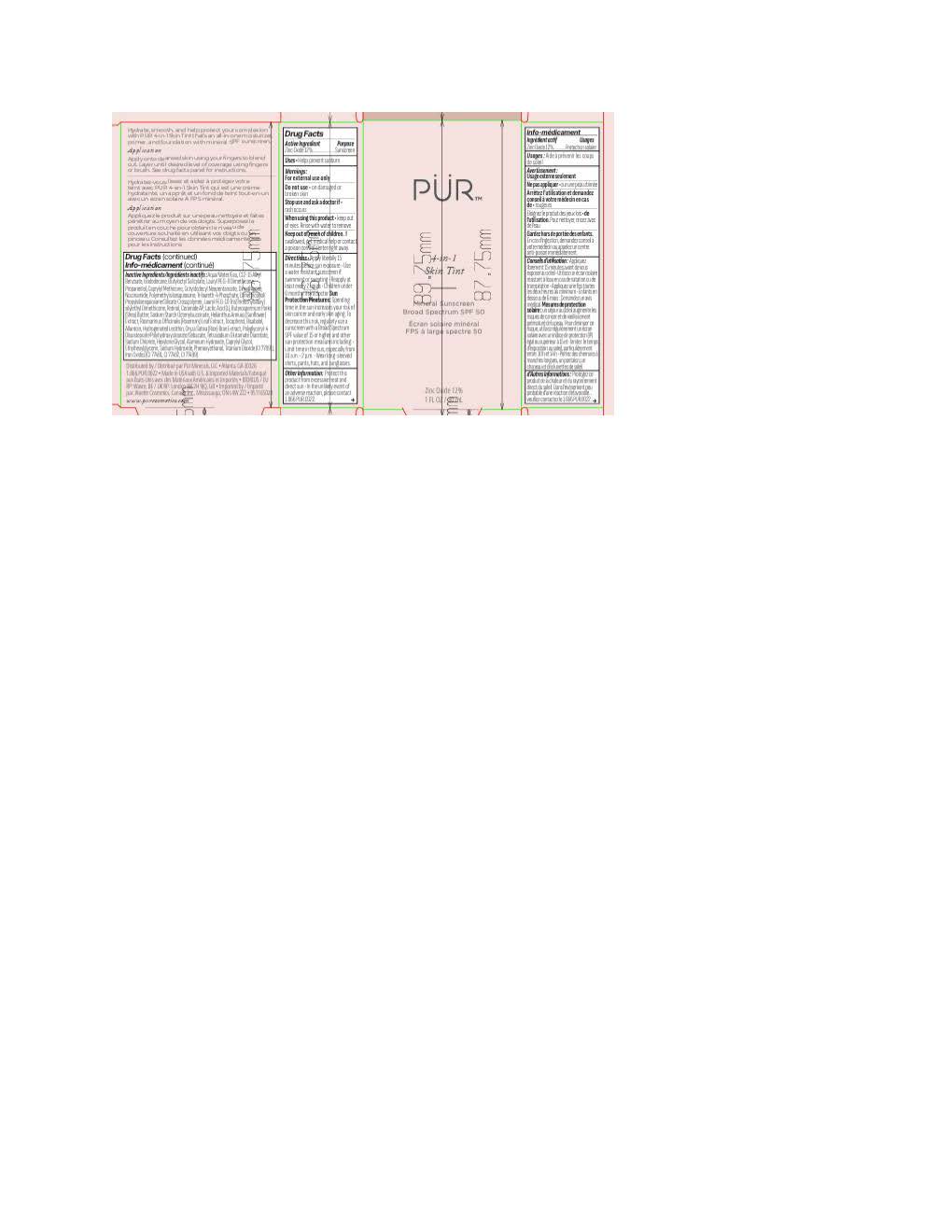 DRUG LABEL: PUR 4-in-1 Skin Tint MN4
NDC: 67345-0053 | Form: LOTION
Manufacturer: PUR Minerals
Category: otc | Type: HUMAN OTC DRUG LABEL
Date: 20250924

ACTIVE INGREDIENTS: ZINC OXIDE 132 mg/1 mL
INACTIVE INGREDIENTS: TOCOPHEROL; RETINOL; ISODODECANE; HELIANTHUS ANNUUS (SUNFLOWER) SEED OIL; HYDROGENATED SOYBEAN LECITHIN; CERAMIDE AP; LACTIC ACID; BUTYROSPERMUM PARKII (SHEA) BUTTER; POLYGLYCERYL-4 DIISOSTEARATE/POLYHYDROXYSTEARATE/SEBACATE; ORYZA SATIVA (RICE) BRAN; SODIUM HYDROXIDE; POLYMETHYLSILSESQUIOXANE (4.5 MICRONS); FERRIC OXIDE YELLOW; ROSMARINUS OFFICINALIS (ROSEMARY) LEAF OIL; TITANIUM DIOXIDE; CAPRYLYL GLYCOL; ALLANTOIN; .ALPHA.-BISABOLOL, (+)-; TRILAURETH-4 PHOSPHATE; BUTYLOCTYL SALICYLATE; NIACINAMIDE; WATER; DIMETHICONOL/PROPYLSILSESQUIOXANE/SILICATE CROSSPOLYMER (450000000 MW); ETHYLHEXYLGLYCERIN; HEXYLENE GLYCOL; PROPANEDIOL; TETRASODIUM GLUTAMATE DIACETATE; SODIUM CHLORIDE; DIMETHICONE; ALKYL (C12-15) BENZOATE; ALUMINUM HYDROXIDE; PHENOXYETHANOL; LAURYL PEG-8 DIMETHICONE (300 CPS); FERRIC OXIDE RED; FERROSOFERRIC OXIDE; OCTYLDODECYL NEOPENTANOATE; CAPRYLYL METHICONE

PUR 4-in-1 Skin Tint MN4